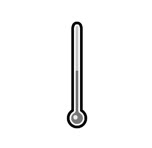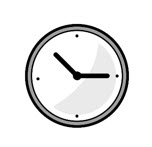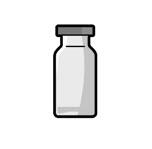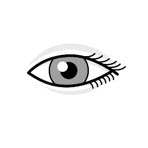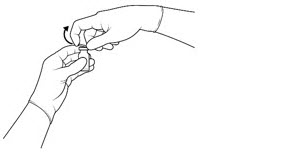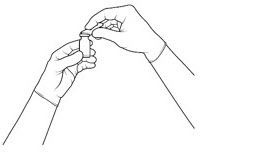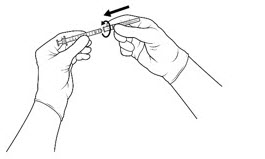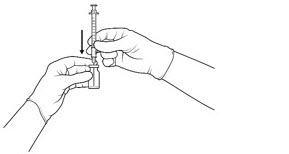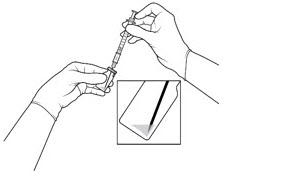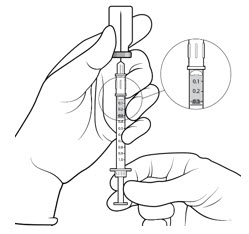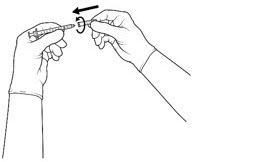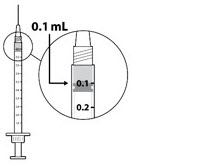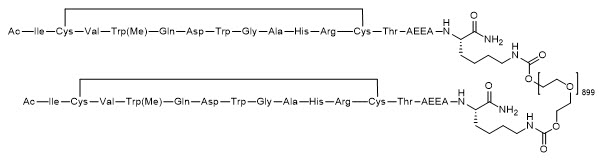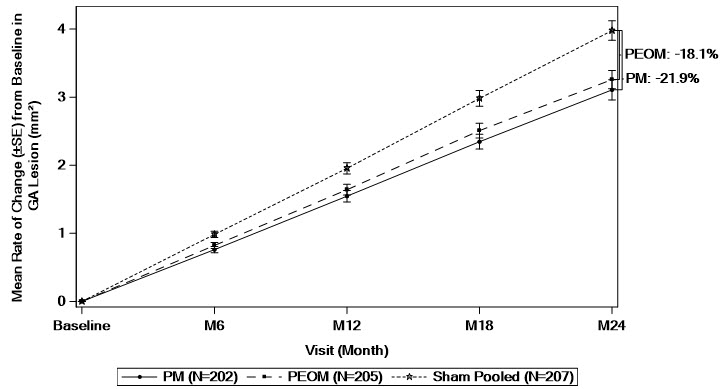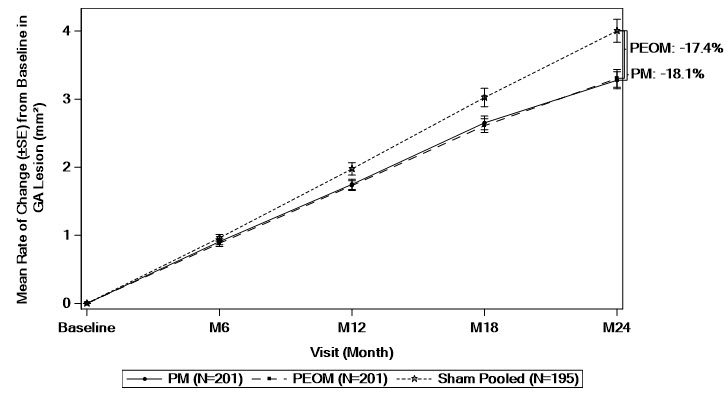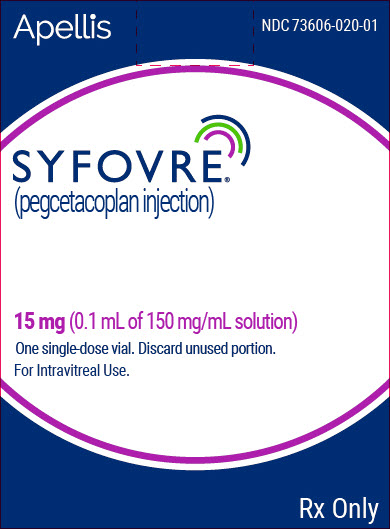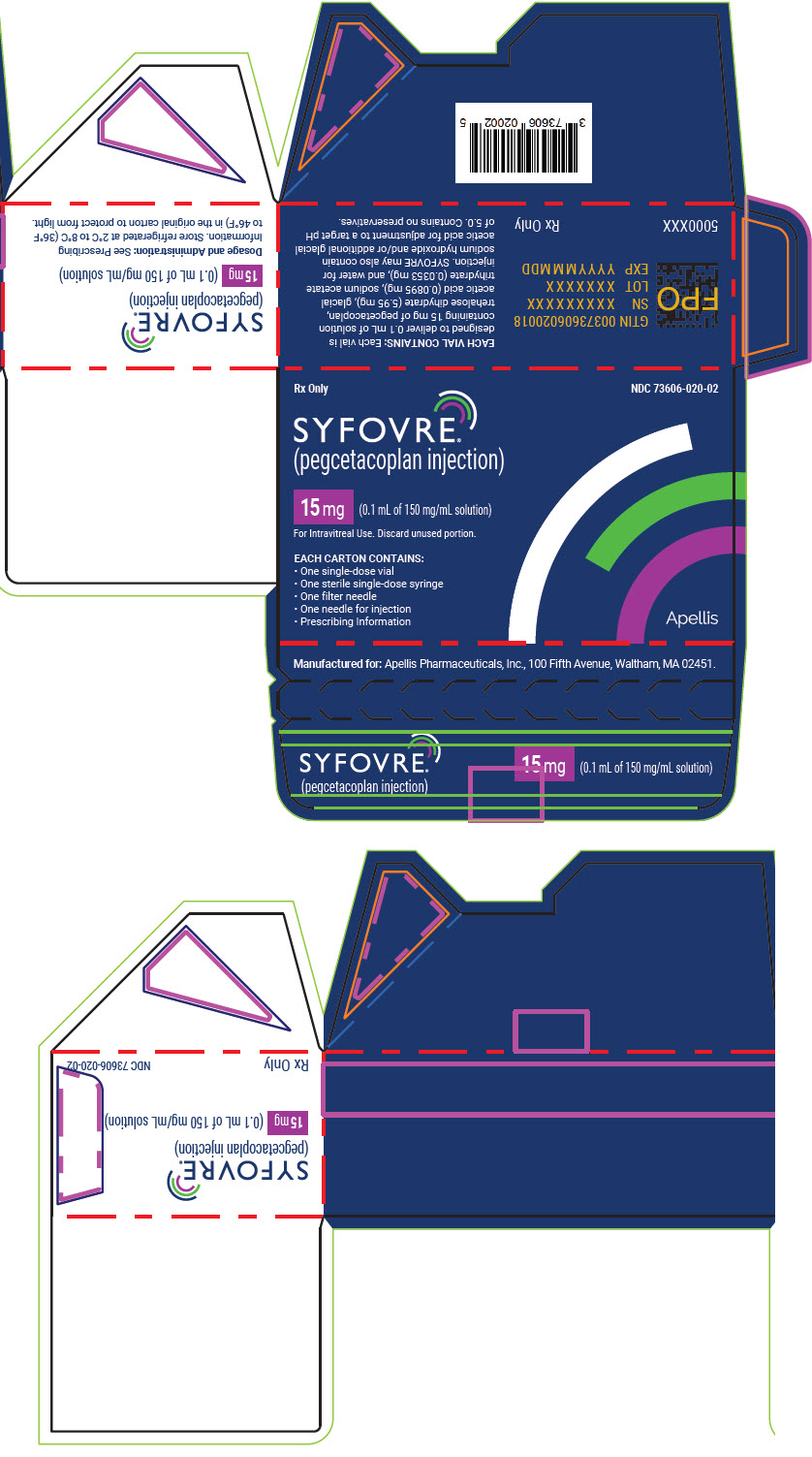 DRUG LABEL: Syfovre
NDC: 73606-020 | Form: INJECTION, SOLUTION
Manufacturer: Apellis Pharmaceuticals, Inc.
Category: prescription | Type: HUMAN PRESCRIPTION DRUG LABEL
Date: 20250916

ACTIVE INGREDIENTS: Pegcetacoplan 15 mg/0.1 mL
INACTIVE INGREDIENTS: Trehalose dihydrate 5.95 mg/0.1 mL; ACETIC ACID; SODIUM ACETATE; Sodium Hydroxide; WATER

HIGHLIGHTS OF PRESCRIBING INFORMATION

These highlights do not include all the information needed to use SYFOVRE safely and effectively. See full prescribing information for SYFOVRE.
SYFOVRE ® (pegcetacoplan injection), for intravitreal use
Initial U.S. Approval: 2021

RECENT MAJOR CHANGES

Dosage and Administration, Preparation for Administration (2.3) | 7/2025
Contraindications, Hypersensitivity (4.3) | 12/2024

1 INDICATIONS AND USAGE

SYFOVRE is a complement inhibitor indicated for the treatment of geographic atrophy (GA) secondary to age-related macular degeneration (AMD). (1)

2 DOSAGE AND ADMINISTRATION

The recommended dose for SYFOVRE is 15 mg (0.1 mL of 150 mg/mL solution) administered by intravitreal injection to each affected eye once every 25 to 60 days. (2.2)

3 DOSAGE FORMS AND STRENGTHS

Injection: 150 mg/mL in a single-dose vial. (3)

4 CONTRAINDICATIONS

- Ocular or Periocular Infections (4.1)
- Active Intraocular Inflammation (4.2)
- Hypersensitivity (4.3)

5 WARNINGS AND PRECAUTIONS

- Endophthalmitis and Retinal Detachments (5.1)
- Retinal Vasculitis and/or Retinal Vascular Occlusion (5.2)
- Neovascular AMD (5.3)
- Intraocular inflammation (5.4)
- Increased Intraocular Pressure (5.5)

6 ADVERSE REACTIONS

Most common adverse reactions (incidence ≥5%) are ocular discomfort, neovascular age-related macular degeneration, vitreous floaters, and conjunctival hemorrhage. (6.1)

To report SUSPECTED ADVERSE REACTIONS, contact Apellis Pharmaceuticals, Inc. at 1-833-866-3346 or FDA at 1-800-FDA-1088 or www.fda.gov/medwatch.

FULL PRESCRIBING INFORMATION

1 INDICATIONS AND USAGE

SYFOVRE is indicated for the treatment of geographic atrophy (GA) secondary to age-related macular degeneration (AMD).

2 DOSAGE AND ADMINISTRATION

2.1 General Dosing Information

SYFOVRE must be administered by a qualified physician.

2.2 Recommended Dosage

The recommended dose for SYFOVRE is 15 mg (0.1 mL of 150 mg/mL solution) administered by intravitreal injection to each affected eye once every 25 to 60 days.

2.3 Preparation for Administration

Store SYFOVRE in the refrigerator between 2°C to 8°C (36°F to 46°F); Keep the vial in the original carton to protect from light.
SYFOVRE is available packaged as follows:

- Vial Only
- Vial Kit with Injection Components (filter needle, syringe, injection needle)

Remove the carton from the refrigerator. Keep the vial in the original carton at room temperature 20°C to 25°C (68°F to 77°F), for at least 15 minutes prior to injection, but no longer than 8 hours. Fill the syringe immediately prior to the injection.

Do not shake the vial.
The vial is for use in a single eye.

Inspect the solution. It is a clear, colorless to light yellow aqueous solution. Do not use if:

- particulates, cloudiness, or discoloration are visible,
- the vial shows signs of damage or tampering,
- the expiration date has passed
- the packaging or components show signs of damage or tampering

STEP 1
Gather the supplies needed:

- One SYFOVRE vial
- One sterile 5-micron filter needle
- One sterile 1-mL Luer-lock syringe with a 0.1 mL dose mark
- One sterile ½ inch: 29-gauge (extra) thin-wall injection needle with Luer-lock hub (included with vial kit) or a 27-gauge needle with Luer-lock hub (not included)
  Note: Increased injection forces and/or increased injection time could be experienced if a smaller diameter injection needle is used (e.g., 30-gauge)
- Alcohol swab (not included)

Use aseptic technique to carry out the following preparation steps:

STEP 2
Remove the flip-off cap from the vial (see Figure 1a) and clean the vial septum with an alcohol swab and wait for the alcohol to dry out (see Figure 1b).

Figure 1a:

Figure 1b:

STEP 3
Attach the 5-micron filter needle onto a 1-mL Luer-lock syringe (see Figure 2) by twisting it onto the Luer-lock syringe tip.

Figure 2:

STEP 4
Push the filter needle into the center of the vial septum until the needle is submerged in the drug product to prevent withdrawal of air (see Figure 3a). To withdraw the entire contents of the vial into the syringe, hold the vial at a slightly inclined position. Withdraw the drug product slowly to prevent air bubbles. Continue to tilt the vial during withdrawal keeping the bevel of the filter needle submerged in the liquid until all of the fluid is withdrawn from the vial (see Figure 3b). *Do not tap the syringe to remove air bubbles. While maintaining the filter needle within the vial, invert the syringe and move the plunger down and up until bubbles move to the top (see Figure 3c).

Figure 3a:

Figure 3b:

Figure 3c:

STEP 5
Using aseptic technique, disconnect the filter needle from the syringe and dispose of it. Do not use the filter needle for injection.

STEP 6
Aseptically and firmly attach the injection needle onto the 1-mL Luer-lock syringe (see Figure 4).

Figure 4:

STEP 7
Check for air bubbles by holding the syringe with the needle pointing up. *Do not tap the syringe to remove air bubbles.
If there are any air bubbles, remove the needle cap and with the needle end facing up gently advance the plunger to the 0.1 mL dose mark (see Figure 5).
Only 0.1 mL (15 mg of SYFOVRE) should be administered to deliver a single dose. Any excess volume should be disposed.
The syringe is ready for injection.

Figure 5:

2.4 Injection Procedure

Only 0.1 mL (15 mg of SYFOVRE) should be administered to deliver a single dose. Any excess volume should be disposed. Ensure that the injection is given immediately after the preparation of the dose.

Prior to the intravitreal injection, patients should be monitored for elevated intraocular pressure (IOP) using tonometry [see Warnings and Precautions (5.4)]. If necessary, ocular hypotensive medication can be given to lower the IOP. The intravitreal injection procedure should be carried out under aseptic conditions, which includes the use of surgical hand disinfection, sterile gloves, a sterile drape, and a sterile eyelid speculum (or equivalent). Adequate anesthesia and a broad-spectrum topical microbicide to disinfect the periocular skin, eyelid, and ocular surface should be administered prior to the injection.

Inject slowly until the rubber stopper reaches the end of the syringe to deliver the volume of 0.1 mL. Confirm delivery of the full dose by checking that the rubber stopper has reached the end of the syringe barrel.

Immediately following the intravitreal injection, patients should be monitored for elevations in IOP. Additional evaluation may include checking for perfusion of the optic nerve head and tonometry.

Following intravitreal injection patients should be instructed to report any symptoms suggestive of endophthalmitis (e.g., eye pain, redness of the eye, photophobia, blurring of vision) without delay [see Patient Counseling Information (17)].

Each vial should only be used for the treatment of a single eye. If the fellow eye requires treatment, a new sterile, vial should be used and the sterile field, syringe, gloves, drapes, eyelid speculum, filter, and injection needles should be changed before SYFOVRE administration. Repeat same procedure steps as above.

Any unused medicinal product or waste material should be disposed of in accordance with local regulations.

3 DOSAGE FORMS AND STRENGTHS

Injection: 150 mg/mL, clear, colorless to light yellow aqueous solution in a single-dose vial for administration of a single 0.1 mL dose.

4 CONTRAINDICATIONS

4.1 Ocular or Periocular Infections

SYFOVRE is contraindicated in patients with ocular or periocular infections [see Warnings and Precautions (5.1)].

4.2 Active Intraocular Inflammation

SYFOVRE is contraindicated in patients with active intraocular inflammation.

4.3 Hypersensitivity

SYFOVRE is contraindicated in patients with hypersensitivity to pegcetacoplan or to any of the excipients in SYFOVRE. Systemic hypersensitivity reactions (e.g., anaphylaxis, rash, urticaria) have occurred in patients treated with SYFOVRE [see Adverse Reactions (6.2)].

5 WARNINGS AND PRECAUTIONS

5.1 Endophthalmitis and Retinal Detachments

Intravitreal injections, including those with SYFOVRE, may be associated with endophthalmitis and retinal detachments [see Adverse Reactions (6.1)]. Proper aseptic injection technique must always be used when administering SYFOVRE in order to minimize the risk of endophthalmitis [see Dosage and Administration (2.4)]. Patients should be instructed to report any symptoms suggestive of endophthalmitis or retinal detachment without delay and should be managed appropriately.

5.2 Retinal Vasculitis and/or Retinal Vascular Occlusion

Retinal vasculitis and/or retinal vascular occlusion, typically in the presence of intraocular inflammation, have been reported with the use of SYFOVRE [see Adverse Reactions (6.2)]. Cases may occur with the first dose of SYFOVRE and may result in severe vision loss. Discontinue treatment with SYFOVRE in patients who develop these events. Patients should be instructed to report any change in vision without delay.

5.3 Neovascular AMD

In clinical trials, use of SYFOVRE was associated with increased rates of neovascular (wet) AMD or choroidal neovascularization (12% when administered monthly, 7% when administered every other month and 3% in the control group) by Month 24. Patients receiving SYFOVRE should be monitored for signs of neovascular AMD. In case anti-Vascular Endothelial Growth Factor (anti-VEGF) is required, it should be given separately from SYFOVRE administration.

5.4 Intraocular Inflammation

In clinical trials, use of SYFOVRE was associated with episodes of intraocular inflammation including: vitritis, vitreal cells, iridocyclitis, uveitis, anterior chamber cells, iritis, and anterior chamber flare. After inflammation resolves patients may resume treatment with SYFOVRE.

5.5 Increased Intraocular Pressure

Acute increase in IOP may occur within minutes of any intravitreal injection, including with SYFOVRE. Perfusion of the optic nerve head should be monitored following the injection and managed as needed [see Dosage and Administration (2.4)].

6 ADVERSE REACTIONS

The following clinically significant adverse reactions are described elsewhere in the labeling:

- Ocular and periocular infections [see Contraindications (4.1)]
- Active intraocular inflammation [see Contraindications (4.2)]
- Hypersensitivity [see Contraindications (4.3)]
- Endophthalmitis and retinal detachments [see Warnings and Precautions (5.1)]
- Retinal Vasculitis and/or Retinal Vascular Occlusion [see Warnings and Precautions (5.2)]
- Neovascular AMD [see Warnings and Precautions (5.3)]
- Intraocular inflammation [see Warnings and Precautions (5.4)]
- Increased intraocular pressure [see Warnings and Precautions (5.5)]

6.1 Clinical Trials Experience

Because clinical trials are conducted under widely varying conditions, adverse reaction rates observed in the clinical trials of a drug cannot be directly compared to rates in the clinical trials of another drug and may not reflect the rates observed in practice.

A total of 839 patients with GA in two Phase 3 studies (OAKS and DERBY) were treated with intravitreal SYFOVRE, 15 mg (0.1 mL of 150 mg/mL solution). Four hundred nineteen (419) of these patients were treated in the affected eye monthly and 420 were treated in the affected eye every other month. Four hundred seventeen (417) patients were assigned to sham.

The most common adverse reactions (≥5%) reported in patients receiving SYFOVRE were ocular discomfort, neovascular age-related macular degeneration, vitreous floaters, and conjunctival hemorrhage.

Table 1: Adverse Reactions in Study Eye Reported in ≥2% of Patients Treated with SYFOVRE Through Month 24 in Studies OAKS and DERBY
Adverse Reactions | PM (N = 419) % | PEOM (N = 420) % | Sham Pooled (N = 417) %
Ocular discomfort [The following reported terms were combined: Ocular discomfort included: eye pain, eye irritation, foreign body sensation in eyes, ocular discomfort, abnormal sensation in eye Neovascular age-related macular degeneration included: exudative age-related macular degeneration, choroidal neovascularization Punctate keratitis included: punctate keratitis, keratitis Intraocular inflammation included: vitritis, vitreal cells, iridocyclitis, uveitis, anterior chamber cells, iritis, anterior chamber flare] | 13 | 10 | 11
Neovascular age-related macular degeneration | 12 | 7 | 3
Vitreous floaters | 10 | 7 | 1
Conjunctival hemorrhage | 8 | 8 | 4
Vitreous detachment | 4 | 6 | 3
Retinal hemorrhage | 4 | 5 | 3
Punctate keratitis | 5 | 3 | <1
Posterior capsule opacification | 4 | 4 | 3
Intraocular inflammation | 4 | 2 | <1
Intraocular pressure increased | 2 | 3 | <1
PM: SYFOVRE monthly; PEOM: SYFOVRE every other month

Endophthalmitis, retinal detachment, hyphema and retinal tears were reported in less than 1% of patients.

Optic ischemic neuropathy was reported in 1.7% of patients treated monthly, 0.2% of patients treated every other month and 0.0% of patients assigned to sham. Deaths were reported in 6.7% of patients treated monthly, 3.6% of patients treated every other month and 3.8% of patients assigned to sham. The rates and causes of death were consistent with the elderly study population.

6.2 Postmarketing Experience

The following adverse reactions have been identified during postapproval use of SYFOVRE. Because these reactions are reported voluntarily from a population of uncertain size, it is not always possible to reliably estimate their frequency or establish a causal relationship to drug exposure.

Eye disorders: retinal vasculitis with or without retinal vascular occlusion.

Systemic reactions: anaphylaxis, rash, and urticaria.

8 USE IN SPECIFIC POPULATIONS

8.1 Pregnancy

Risk Summary

There are no adequate and well-controlled studies of SYFOVRE administration in pregnant women to inform a drug-associated risk. The use of SYFOVRE may be considered following an assessment of the risks and benefits.

Systemic exposure of SYFOVRE following ocular administration is low [see Clinical Pharmacology (12.3)]. Subcutaneous administration of pegcetacoplan to pregnant monkeys from the mid gestation period through birth resulted in increased incidences of abortions and stillbirths at systemic exposures 1040-fold higher than that observed in humans at the maximum recommended human ophthalmic dose (MRHOD) of SYFOVRE (based on the area under the curve (AUC) systemically measured levels). No adverse maternal or fetal effects were observed in monkeys at systemic exposures approximately 470-fold higher than that observed in humans at the MRHOD (see Data).

In the U.S. general population, the estimated background risk of major birth defects and miscarriage in clinically recognized pregnancies is 2-4% and 15-20%, respectively.

Data

Animal Data

In embryofetal development studies, subcutaneous administration of pegcetacoplan to pregnant cynomolgus monkeys from the mid gestation period through birth produced increased incidences of abortions and stillbirths at doses of 28 mg/kg/day [approximately 1040-fold higher than the MRHOD based on exposure (AUC)]. Pegcetacoplan was not maternally toxic and did not produce adverse embryofetal effects in the monkey at subcutaneous doses of 7 mg/kg/day. (approximately 470-fold higher than the MRHOD). No developmental effects were observed in infants up to 6 months postpartum. Minimal systemic exposure to pegcetacoplan (less than 1%, not pharmacologically significant) was detected in fetuses from monkeys treated subcutaneously with 28 mg/kg/day from the period of organogenesis through the second trimester.

8.2 Lactation

Risk Summary

It is not known whether intravitreal administered pegcetacoplan is secreted in human milk or whether there is potential for absorption and harm to the infant. Animal data suggest that the risk of clinically relevant exposure to the infant following maternal intravitreal treatment is minimal (see Data). Because many drugs are excreted in human milk, and because the potential for absorption and harm to infant growth and development exists, caution should be exercised when SYFOVRE is administered to a nursing woman.

Data

Animal Data

Pegcetacoplan was detectable in milk of lactating monkeys after subcutaneous administration at less than 1% concentration of serum levels but was not detectable in the serum of nursing infants.

8.3 Females and Males of Reproductive Potential

Contraception

Females

It is recommended that women of childbearing potential use effective contraception methods to prevent pregnancy during treatment with intravitreal pegcetacoplan. Advise female patients of reproductive potential to use effective contraception during treatment with SYFOVRE and for 40 days after the last dose. For women planning to become pregnant, the use of SYFOVRE may be considered following an assessment of the risks and benefits.

8.4 Pediatric Use

The safety and effectiveness of SYFOVRE in pediatric patients have not been established.

8.5 Geriatric Use

In clinical studies, approximately 97% (813/839) of patients randomized to treatment with SYFOVRE were ≥ 65 years of age and approximately 72% (607/839) were ≥ 75 years of age. No significant differences in efficacy or safety were seen with increasing age in these studies. No dosage regimen adjustment is recommended based on age.

11 DESCRIPTION

SYFOVRE contains pegcetacoplan, a complement inhibitor. Pegcetacoplan is a symmetrical molecule composed of two identical pentadecapeptides covalently bound to the ends of a linear 40 kiloDalton (kDa) polyethylene glycol (PEG) molecule. The peptide portions of pegcetacoplan contain 1-methyl-L-tryptophan (Trp(Me)) in position 4 and amino (ethoxyethoxy) acetic acid (AEEA) in position 14.

The molecular weight of pegcetacoplan is approximately 43.5 kDa. The molecular formula is C1970H3848N50O947S4. The structure of pegcetacoplan is shown below.

SYFOVRE (pegcetacoplan injection) is a sterile, clear, colorless to light yellow aqueous solution in a single-dose vial for intravitreal use. Each vial allows for the delivery of 0.1 mL of solution containing 15 mg pegcetacoplan, trehalose dihydrate (5.95 mg), glacial acetic acid (0.0895 mg), sodium acetate trihydrate (0.0353 mg), and Water for Injection. SYFOVRE may also contain sodium hydroxide and/or additional glacial acetic acid for adjustment to a target pH of 5.0. SYFOVRE does not contain an anti-microbial preservative.

12 CLINICAL PHARMACOLOGY

12.1 Mechanism of Action

Pegcetacoplan binds to complement protein C3 and its activation fragment C3b with high affinity thereby regulating the cleavage of C3 and the generation of downstream effectors of complement activation

12.2 Pharmacodynamics

Cardiac Electrophysiology

Subcutaneous (SC) dosing of pegcetacoplan did not result in QT prolongation. Systemic exposures following intravitreal (IVT) administration are much lower than with SC administration, therefore QT prolongation following IVT pegcetacoplan is not expected.

12.3 Pharmacokinetics

SYFOVRE is administered directly into the vitreous to exert local effects in the eye.

Following repeat intravitreal administration of pegcetacoplan at a dose of 15 mg, geometric mean (%CV) serum Cmax value at steady state was 2.2 μg/mL (28.7%) and 1.5 μg/mL (58.1%) for GA patients dosed monthly and every other month, respectively. The steady state geometric mean (%CV) serum trough concentrations were 1.0 μg/mL (52.3%) and 0.2 μg/mL (89.6%) for patients treated monthly and every other month, respectively.

Absorption

Following intravitreal administration of pegcetacoplan, the systemic median Tmax of pegcetacoplan is between 7 and 14 days. Following intravitreal treatment, systemic exposure of pegcetacoplan increases approximately proportionally over a dosage range from 4 to 20 mg.

Distribution

The geometric mean (95%CI) volume of distribution of pegcetacoplan is approximately 1.85 L (1.62 - 2.12) in patients with GA following intravitreal administration.

Elimination

The estimated geometric mean (%CV) of clearance (CL) is 0.284 L/day (21.1%) and geometric mean half-life of elimination (t1/2) is 4.5 days (21.1%) in patients with GA.

Metabolism

Pegcetacoplan is expected to be metabolized into small peptides and amino acids by catabolic pathways.

Specific Populations

There were no clinically significant differences on the pharmacokinetics of pegcetacoplan intravitreal administration based on age (60 to 97 years old), gender, renal impairment, and hepatic function as evaluated by total bilirubin (0.05-1.7 mg/dL), albumin (2.96-5.38 g/dL), aspartate aminotransferase (8.7-101 IU/L), or alanine aminotransferase (5.9-136 IU/L).

12.6 Immunogenicity

The observed incidence of anti-drug antibodies (ADA) is highly dependent on the sensitivity and specificity of the assay. Difference in assay methods preclude meaningful comparisons of the incidence of ADA in the studies described below with the incidence of ADA in other studies.

In the 24-month period in studies OAKS and DERBY, the incidence of anti-pegcetacoplan peptide antibodies in patients treated with pegcetacoplan was 4% (18/415 evaluable patients) and 2.5% (10/404 evaluable patients), respectively. Because of the low incidence of anti-pegcetacoplan peptide antibodies, the effect of these antibodies on the pharmacokinetics, pharmacodynamics, safety, and/or effectiveness of pegcetacoplan is unknown.

13 NONCLINICAL TOXICOLOGY

13.1 Carcinogenesis, Mutagenesis, Impairment of Fertility

Carcinogenesis

Animal carcinogenicity studies of pegcetacoplan have not been conducted.

Mutagenesis

Pegcetacoplan was not mutagenic when tested in in vitro bacterial reverse mutation (Ames) assays and was not genotoxic in an in vitro assay in human TK6 cells or in an in vivo micronucleus assay in mice.

Impairment of Fertility

There are no fertility data in humans or animals. There were no microscopic abnormalities in male or female reproductive organs in toxicity studies in rabbits and monkeys indicative of an impact of pegcetacoplan on fertility.

14 CLINICAL STUDIES

The safety and efficacy of SYFOVRE were assessed in two multi-center, randomized, sham-controlled studies in patients with GA (atrophic nonexudative age-related macular degeneration), with or without subfoveal involvement, secondary to AMD in a total of 1258 randomized patients (SYFOVRE 839 patients, sham 419 patients). Studies OAKS (APL2-304; NCT03525613) and DERBY (APL2-303; NCT03525600) were 24 months in duration, in which patients received treatment for the entire length of the study.

Patient ages ranged from 60 to 100 years with a mean of 78.7 years. Mean (standard deviation) total area of GA lesions(s) at baseline in the study eye (in mm^2) were 8.23 (3.83) and 8.29 (4.11) for OAKS and DERBY respectively.

In each study, patients were randomly assigned in a 2:2:1:1 ratio to 1 of 4 dosing regimens:

- 1) SYFOVRE administered at 15 mg/0.1 mL monthly;
- 2) SYFOVRE administered at 15 mg/0.1 mL every other month;
- 3) sham administered monthly;
- 4) sham administered every other month.

In OAKS, 31% of patients in the monthly group, 21% of patients in the every other month and 25% of the patients assigned to sham discontinued treatment prior to Month 24. In DERBY, 29% of patients in the monthly group, 22% of patients in the every other month and 21% of the patients assigned to sham discontinued treatment prior to Month 24.

There was a reduction in the mean rate of GA lesion growth observed in both studies.

Detailed results are shown in Table 2 and Figures 1 and 2.

Table 2: Analysis of Change from Baseline in Study Eye GA Lesion Area Measured by FAF in Studies OAKS and DERBY
Time Period | Group | Rate of GA Lesion Area Growth (mm^2) [Based on a mixed effects model for repeated measures assuming a piecewise linear trend in time with knots at Month 6, Month 12, and Month 18. The model included effects for treatment, baseline GA lesion area (<7.5 mm^2 or ≥7.5 mm^2), time terms, presence of choroidal neovascularization in the fellow eye (yes or no), time terms by treatment interactions, and time terms by baseline GA lesion area (<7.5 mm^2 or ≥7.5 mm^2) interactions. Time terms include a linear effect of time for each 6-month time period.]
Time Period | Group | Slope (SE) | Difference (95% CI) in Slope from Sham Pooled | Percent Difference from Sham Pooled
OAKS (PM: N=202; PEOM: N=205; Sham Pooled: N=207)
Baseline to Month 24 [Slope for baseline to Month 24 is an average of slope of baseline to Month 6, Month 6 to Month 12, Month 12 to Month 18, and Month 18 to Month 24.] | PM | 3.11 (0.148) | −0.87 (−1.27 to −0.47) | −21.9%
Baseline to Month 24 [Slope for baseline to Month 24 is an average of slope of baseline to Month 6, Month 6 to Month 12, Month 12 to Month 18, and Month 18 to Month 24.] | PEOM | 3.26 (0.134) | −0.72 (−1.10 to −0.33) | −18.1%
Baseline to Month 24 [Slope for baseline to Month 24 is an average of slope of baseline to Month 6, Month 6 to Month 12, Month 12 to Month 18, and Month 18 to Month 24.] | Sham Pooled | 3.98 (0.143) | NA
Baseline to Month 6 | PM | 0.76 (0.046) | −0.22 (−0.35 to −0.09) | −22.7%
Baseline to Month 6 | PEOM | 0.82 (0.043) | −0.16 (−0.29 to −0.04) | −16.4%
Baseline to Month 6 | Sham Pooled | 0.98 (0.047) | NA
Month 6 to Month 12 | PM | 0.78 (0.060) | −0.19 (−0.34 to −0.03) | −19.2%
Month 6 to Month 12 | PEOM | 0.82 (0.057) | −0.15 (−0.30 to −0.00) | −15.7%
Month 6 to Month 12 | Sham Pooled | 0.97 (0.052) | NA
Month 12 to Month 18 | PM | 0.80 (0.050) | −0.23 (−0.37 to −0.08) | −22.1%
Month 12 to Month 18 | PEOM | 0.87 (0.050) | −0.16 (−0.30 to −0.02) | −15.4%
Month 12 to Month 18 | Sham Pooled | 1.03 (0.053) | NA
Month 18 to Month 24 | PM | 0.76 (0.067) | −0.23 (−0.41 to −0.06) | −23.5%
Month 18 to Month 24 | PEOM | 0.75 (0.044) | −0.25 (−0.39 to −0.10) | −24.7%
Month 18 to Month 24 | Sham Pooled | 1.00 (0.058) | NA
DERBY (PM: N=201; PEOM: N=201; Sham Pooled: N=195)
Baseline to Month 24 | PM | 3.28 (0.125) | −0.73 (−1.14 to −0.31) | −18.1%
Baseline to Month 24 | PEOM | 3.31 (0.129) | −0.70 (−1.11 to −0.28) | −17.4%
Baseline to Month 24 | Sham Pooled | 4.00 (0.169) | NA
Baseline to Month 6 | PM | 0.91 (0.048) | −0.05 (−0.19 to 0.08) | −5.7%
Baseline to Month 6 | PEOM | 0.88 (0.047) | −0.08 (−0.21 to 0.05) | −8.2%
Baseline to Month 6 | Sham Pooled | 0.96 (0.050) | NA
Month 6 to Month 12 | PM | 0.84 (0.051) | −0.17 (−0.33 to −0.02) | −17.0%
Month 6 to Month 12 | PEOM | 0.85 (0.051) | −0.17 (−0.32 to −0.01) | −16.4%
Month 6 to Month 12 | Sham Pooled | 1.01 (0.060) | NA
Month 12 to Month 18 | PM | 0.90 (0.049) | −0.14 (−0.29 to 0.00) | −13.8%
Month 12 to Month 18 | PEOM | 0.88 (0.051) | −0.17 (−0.32 to −0.02) | −16.0%
Month 12 to Month 18 | Sham Pooled | 1.05 (0.056) | NA
Month 18 to Month 24 | PM | 0.63 (0.068) | −0.35 (−0.52 to −0.18) | −36.1%
Month 18 to Month 24 | PEOM | 0.69 (0.053) | −0.28 (−0.43 to −0.14) | −29.1%
Month 18 to Month 24 | Sham Pooled | 0.98 (0.055) | NA
GA: Geographic atrophy; FAF: fundus autofluorescence; PM: SYFOVRE monthly; PEOM: SYFOVRE every other month; SE: standard error; CI: confidence interval

Figure 1: Mean Rate of Change from Baseline in Study Eye GA Lesion Area Measured by FAF in OAKS

GA: Geographic atrophy; FAF: fundus autofluorescence; PM: SYFOVRE monthly; PEOM: SYFOVRE every other month; SE: standard error.
Based on a mixed effects model for repeated measures assuming a piecewise linear trend in time with knots at Month 6, Month 12, and Month 18. The model included effects for treatment, baseline GA lesion area (<7.5 mm^2 or ≥7.5 mm^2), time terms, presence of choroidal neovascularization in the fellow eye (yes or no), time terms by treatment interactions, and time terms by baseline GA lesion area (<7.5 mm^2 or ≥7.5 mm^2) interactions. Time terms include a linear effect of time for each 6-month time period.

Figure 2: Mean Rate of Change from Baseline in Study Eye GA Lesion Area Measured by FAF in DERBY

GA: Geographic atrophy; FAF: fundus autofluorescence; PM: SYFOVRE monthly; PEOM: SYFOVRE every other month; SE: standard error.
Based on a mixed effects model for repeated measures assuming a piecewise linear trend in time with knots at Month 6, Month 12, and Month 18. The model included effects for treatment, baseline GA lesion area (<7.5 mm^2 or ≥7.5 mm^2), time terms, presence of choroidal neovascularization in the fellow eye (yes or no), time terms by treatment interactions, and time terms by baseline GA lesion area (<7.5 mm^2 or ≥7.5 mm^2) interactions. Time terms include a linear effect of time for each 6-month time period.

16 HOW SUPPLIED/STORAGE AND HANDLING

16.1 How Supplied

SYFOVRE (pegcetacoplan injection) is supplied as a clear, colorless to light yellow aqueous solution. Each glass vial contains an overfill amount to allow for administration of a single 0.1 mL dose of solution containing 15 mg of SYFOVRE.

SYFOVRE packaging options are included in Table 3.

Table 3: Packaging Options
NDC Number | Carton Type | Carton Contents
73606-020-02 | Vial Kit with Injection Components | - One SYFOVRE vial - One sterile 5-micron filter needle - One sterile 1-mL Luer-lock syringe with a 0.1 mL dose mark - One sterile ½ inch: 29-gauge extra thin-wall injection needle with Luer-lock - One prescribing information
73606-020-01 | Vial Only | - One SYFOVRE vial - One prescribing information

16.2 Storage and Handling

Refrigerate SYFOVRE between 2°C to 8°C (36°F to 46°F). Store the vial in the original carton to protect from light.

Do not use beyond the expiration date on the carton.

Do not shake.

17 PATIENT COUNSELING INFORMATION

Advise patients that following SYFOVRE administration, patients are at risk of developing endophthalmitis, retinal detachments, retinal vasculitis with or without retinal vascular occlusion and neovascular AMD. If the eye becomes red, sensitive to light, painful, or if a patient develops any change in vision such as flashing lights, blurred vision or metamorphopsia, instruct the patient to seek immediate care from an ophthalmologist [see Warnings and Precautions (5.1, 5.2, 5.3)].

Patients may experience temporary visual disturbances associated either with the intravitreal injection with SYFOVRE or the eye examination [see Adverse Reactions (6.1)]. Advise patients not to drive or use machinery until visual function has recovered sufficiently.

Manufactured for:
Apellis Pharmaceuticals, Inc.
100 Fifth Avenue
Waltham, MA 02451

For patent information: www.apellis.com/productpatent

Copyright © 2025 Apellis Pharmaceuticals, Inc. All rights reserved.
SYFOVRE is a registered trademark of Apellis Pharmaceuticals, Inc.

SYF-PI-25Jul2025-4.0

PRINCIPAL DISPLAY PANEL - 15 mg Vial Carton

Apellis

NDC 73606-020-01

SYFOVRE®
(pegcetacoplan injection)

15 mg (0.1 mL of 150 mg/mL solution)

One single-dose vial. Discard unused portion.

For Intravitreal Use.

Rx Only

PRINCIPAL DISPLAY PANEL - 15 mg Vial Carton - Kit Package

Rx Only

NDC 73606-020-02

SYFOVRE®
(pegcetacoplan injection)

15 mg (0.1 mL of 150 mg/mL solution)

For Intravitreal Use. Discard unused portion.

EACH CARTON CONTAINS:

- One single-dose vial
- One sterile single-dose syringe
- One filter needle
- One needle for injection
- Prescribing Information

Apellis